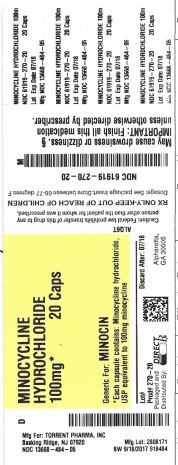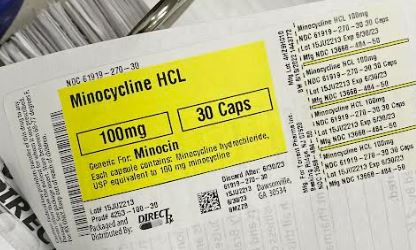 DRUG LABEL: MINOCYCLINE HYDROCHLORIDE
NDC: 61919-270 | Form: CAPSULE
Manufacturer: DirectRX
Category: prescription | Type: HUMAN PRESCRIPTION DRUG LABEL
Date: 20230417

ACTIVE INGREDIENTS: MINOCYCLINE HYDROCHLORIDE 100 mg/1 1
INACTIVE INGREDIENTS: MAGNESIUM STEARATE; STARCH, CORN; FERROSOFERRIC OXIDE; SHELLAC; GELATIN; POTASSIUM HYDROXIDE; TITANIUM DIOXIDE; PROPYLENE GLYCOL

MINOCYCLINE HYDROCHLORIDE

SPL Unclassified

Rx only

To reduce the development of drug-resistant bacteria and maintain the effectiveness of minocycline hydrochloride capsules, USP and other antibacterial drugs, minocycline hydrochloride capsules, USP should be used only to treat or prevent infections that are proven or strongly suspected to be caused by bacteria.